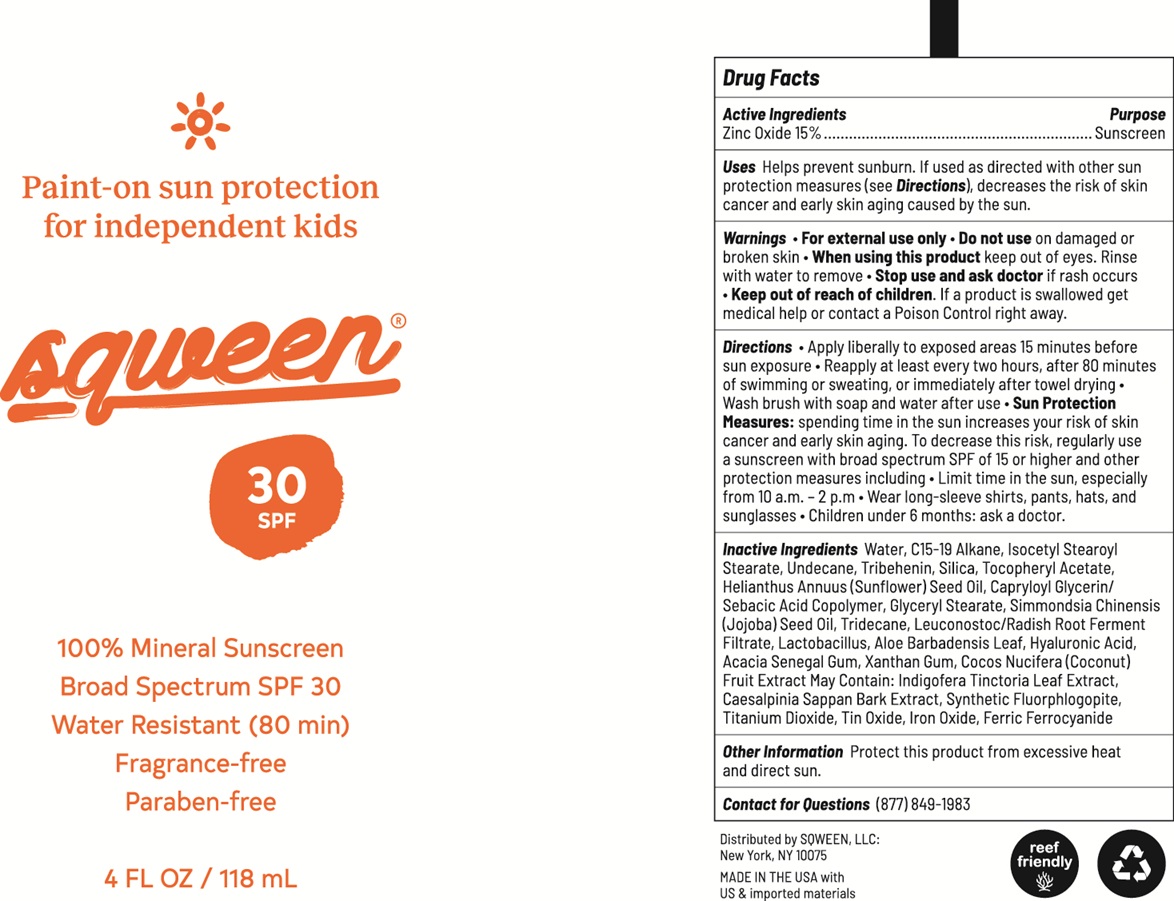 DRUG LABEL: Sqween Paint-On Sun Protection for Independent Kids Mineral Sunscreen SPF 30
NDC: 83005-0002 | Form: CREAM
Manufacturer: Sqween LLC
Category: otc | Type: HUMAN OTC DRUG LABEL
Date: 20260114

ACTIVE INGREDIENTS: ZINC OXIDE 150 mg/1 mL
INACTIVE INGREDIENTS: WATER; C15-19 ALKANE; ISOCETYL STEAROYL STEARATE; UNDECANE; TRIBEHENIN; SILICON DIOXIDE; .ALPHA.-TOCOPHEROL ACETATE; HELIANTHUS ANNUUS FLOWERING TOP; GLYCERYL MONOSTEARATE; JOJOBA OIL; TRIDECANE; BIFIDOBACTERIUM ANIMALIS LACTIS; LEUCONOSTOC/RADISH ROOT FERMENT FILTRATE; ALOE VERA LEAF; HYALURONIC ACID; ACACIA; XANTHAN GUM; COCONUT

Sqween Paint-On Sun Protection for Independent Kids Mineral Sunscreen SPF 30

Active Ingredients

Zinc Oxide 15%

Purpose

Sunscreen

Uses

Helps prevent sunburn. If used as directed with other sun protection measures (see Direction), decreases the risk of skin cancer and early skin aging caused by the sun.

Warnings

- For external use only

Do not use

- On damaged or brocken skin

When using this product

- keep out of eyes. Rinse with water to remove

Stop use and adk doctor

- if rash occurs

Keep out of reach of children.

- If product is swallowed get medical help or contact a poison Control right away.

Directons

- Apply liberally to exposed areas 15 minutes before sun exposure
- Repply at least every two hours, after 80 minutes of swimming or sweating, or immediately after towel dryling Wash brush with soap and water after use

- Sun Protection Measure: spending time in the sun increases your risk of skin cancer and early skin aging. To decreases this risk, regularly use a sunscreen with broad spectrum SPF of higher and other protection, easures including
- Limit time in the sun, especially from 10 a.m - 2 p.m
- Wear long -sleeve shirts, pants hats, and sunglasses
- Children under 6 months: ask a doctor.

Inactive Ingredients

Water, C15-19 Alkane, Isocetyl Stearoyl Stearate, Undecane, Tribehenin, Silica, Tocopheryl Acetate, Helianthus Annus (Sunflower) Seed Oil, Capryloyl Glycerin/Sebacic Acid Copolymer, Glyceryl Stearate, Simmondsia Chinensis (Jojoba|) Seed Oil, Tridecane, Leuconostoc/Radish Root Ferment Filtrate, Lactobacillus, Aloe Barbadensis Leaf, Hyaluronic Acid, Acacia Senegal Gum, Xanthan Gum, Cocos Nucifera (Coconut) Fruit Extract May Contain: Indigofera Tinctoria Leaf Extract, Caesalpinia Sappan Bark Extract, Synthetic Fluorphlogopite, Titanium Dioxide, Tin Oxide, Iron Oxide, Ferric Ferrocyanide

Other Information

Protect this product from excessive heat and direct sun.

Contact for Questions

(877) 849-1983